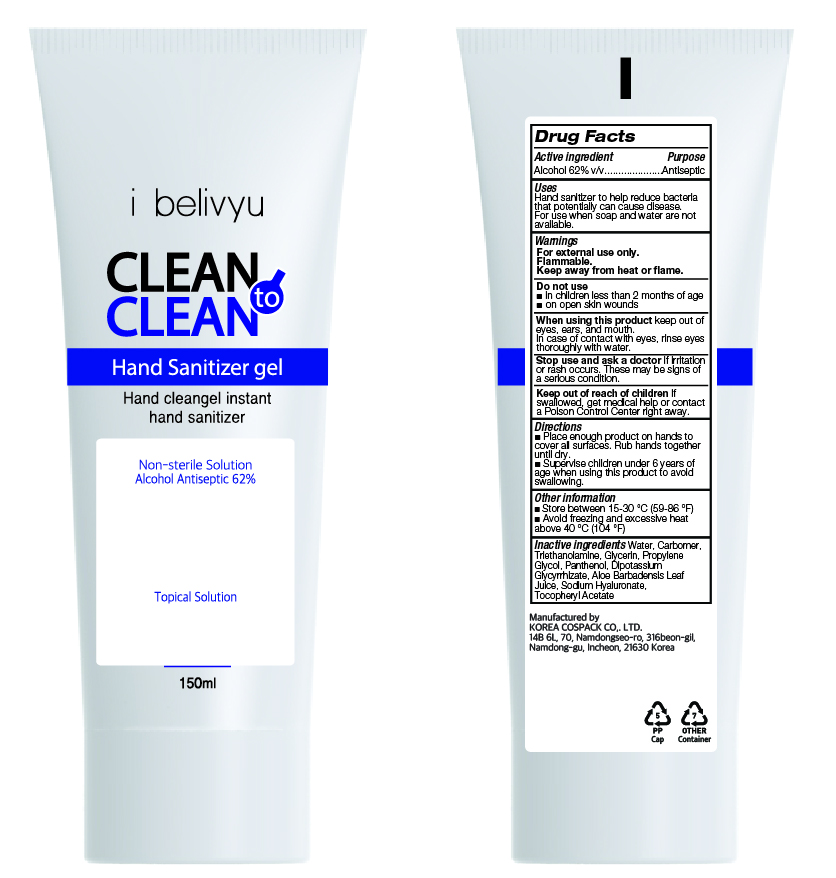 DRUG LABEL: CLEAN TO CLEAN HAND SANITIZER Gel
NDC: 74064-0150 | Form: GEL
Manufacturer: KOREA COSPACK CO.,LTD.
Category: otc | Type: HUMAN OTC DRUG LABEL
Date: 20200411

ACTIVE INGREDIENTS: ALCOHOL 93 mL/150 mL
INACTIVE INGREDIENTS: GLYCERIN; CARBOMER HOMOPOLYMER, UNSPECIFIED TYPE; WATER; PROPYLENE GLYCOL; PANTHENOL; GLYCYRRHIZINATE DIPOTASSIUM; ALOE VERA LEAF; .ALPHA.-TOCOPHEROL ACETATE; HYALURONATE SODIUM; TROLAMINE

[CLEAN TO CLEAN HAND SANITIZER Gel] 150 ml : 74064-0150